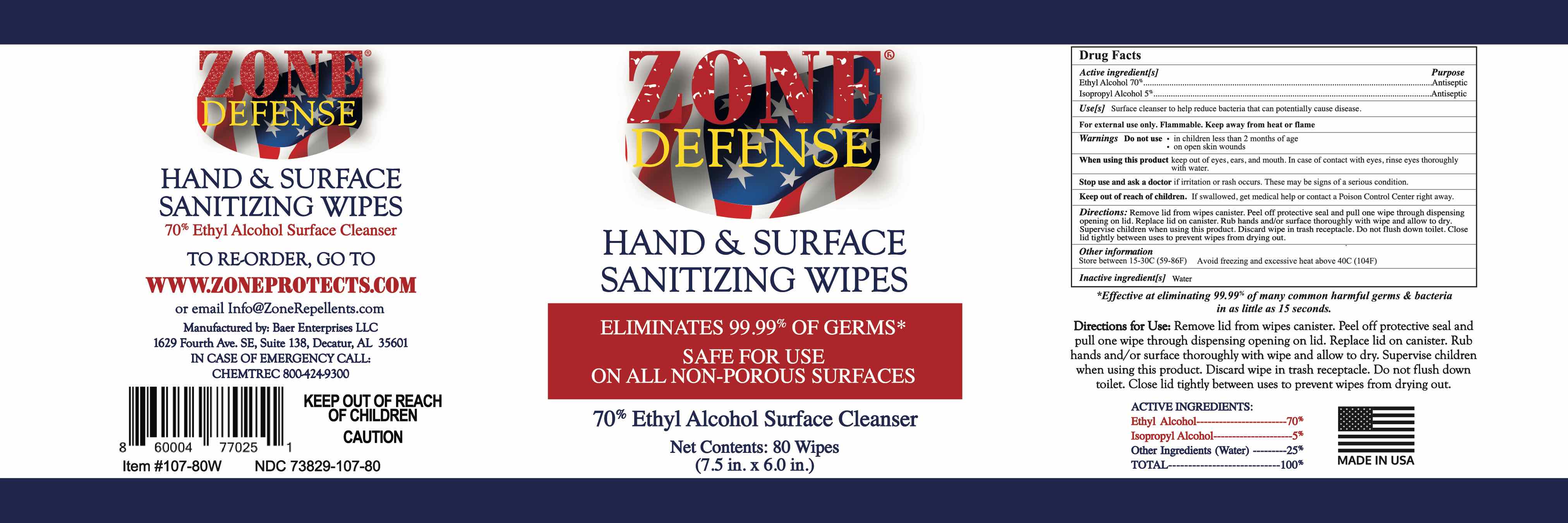 DRUG LABEL: Zone Defense Hand and Surface Sanitizing Wipes
NDC: 73829-107 | Form: CLOTH
Manufacturer: Baer Enterprises, LLC
Category: otc | Type: HUMAN OTC DRUG LABEL
Date: 20220124

ACTIVE INGREDIENTS: ISOPROPYL ALCOHOL 5 mL/100 mL; ALCOHOL 70 mL/100 mL
INACTIVE INGREDIENTS: WATER 25 mL/100 mL

Active Ingredient(s)

Ethyl Alcohol 70% v/v. Purpose: Antiseptic

Isopropyl Alcohol 5% v/v Purpose: Antiseptic

Purpose

Antiseptic, Hand Sanitizer

Use

Hand and Surface Cleanser to help reduce bacteria that can potentially cause disease.

Warnings

For external use only. Flammable. Keep away from heat or flame

Do not use

- in children less than 2 months of age
- on open skin wounds

When using this product keep out of eyes, ears, and mouth. In case of contact with eyes, rinse eyes thoroughly with water.
Stop use and ask a doctor if irritation or rash occurs. These may be signs of a serious condition.
Keep out of reach of children. If swallowed, get medical help or contact a Poison Control Center right away.

Stop use and ask a doctor if irritation or rash occurs. These may be signs of a serious condition.

Keep out of reach of children. If swallowed, get medical help or contact a Poison Control Center right away.

Directions

- Rub hands and/or surface thoroughly with wipe and allow to dry.
- Supervise children under 6 years of age when using this product.
- Discard wipe in trach receptacle
- Do no flush down toilet.

Other information

- Store between 15-30C (59-86F)
- Avoid freezing and excessive heat above 40C (104F)

Inactive ingredients

Water.